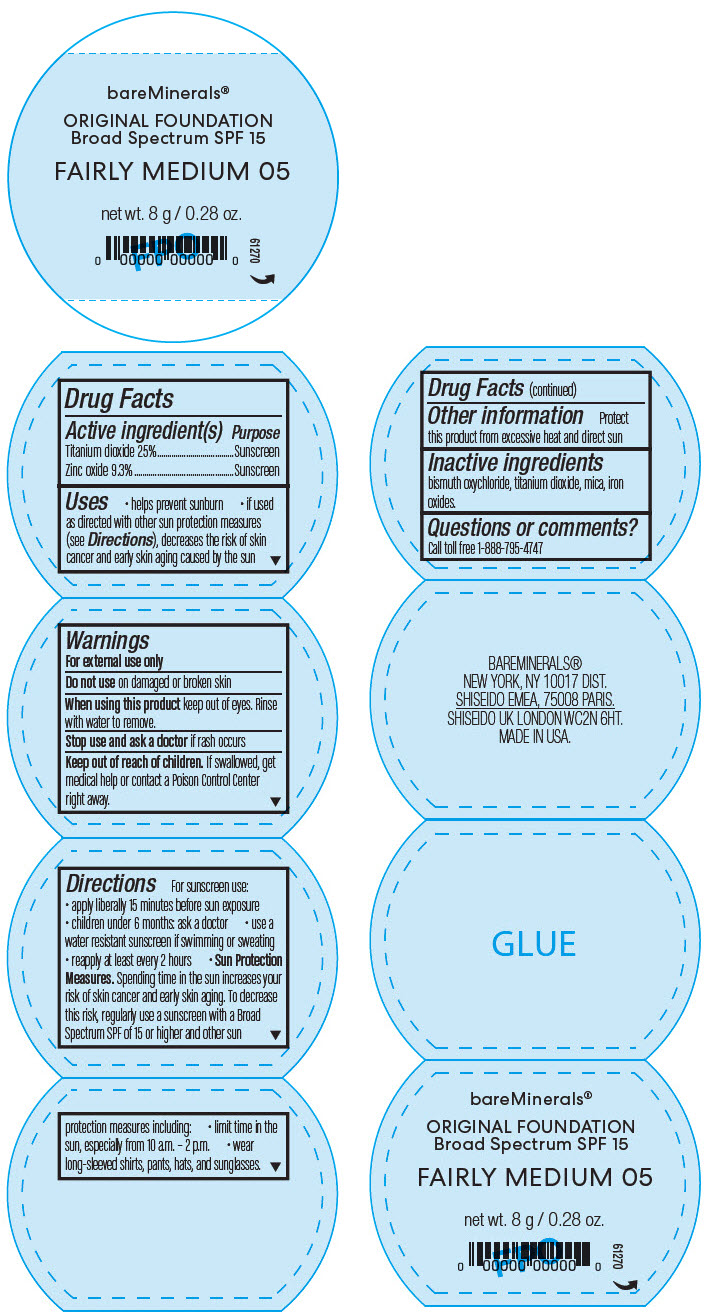 DRUG LABEL: bareMinerals Original Foundation Broad Spectrum SPF 15
NDC: 98132-018 | Form: POWDER
Manufacturer: Orveon Global US LLC
Category: otc | Type: HUMAN OTC DRUG LABEL
Date: 20231004

ACTIVE INGREDIENTS: TITANIUM DIOXIDE 2000 mg/8 g; ZINC OXIDE 744 mg/8 g
INACTIVE INGREDIENTS: MICA; FERRIC OXIDE RED; BISMUTH OXYCHLORIDE

bareMinerals® Original Foundation Broad Spectrum SPF 15
Fairly Medium 05

Drug Facts

ACTIVE INGREDIENT

Active ingredient(s) | Purpose
Titanium dioxide 25% | Sunscreen
Zinc oxide 9.3% | Sunscreen

Uses

- helps prevent sunburn
- if used as directed with other sun protection measures (see Directions), decreases the risk of skin cancer and early skin aging caused by the sun

Warnings

For external use only

Do not use on damaged or broken skin

When using this product keep out of eyes. Rinse with water to remove.

Stop use and ask a doctor if rash occurs

Keep out of reach of children. If swallowed, get medical help or contact a Poison Control Center right away.

Directions

For sunscreen use:

- apply liberally 15 minutes before sun exposure
- children under 6 months: ask a doctor
- use a water resistant sunscreen if swimming or sweating
- reapply at least every 2 hours
- Sun Protection Measures. Spending time in the sun increases your risk of skin cancer and early skin aging. To decrease this risk, regularly use a sunscreen with a Broad Spectrum SPF of 15 or higher and other sun protection measures including:
  - limit time in the sun, especially from 10 a.m. – 2 p.m.
  - wear long-sleeved shirts, pants, hats, and sunglasses.

Other information

Protect this product from excessive heat and direct sun

Inactive ingredients

bismuth oxychloride, titanium dioxide, mica, iron oxides.

Questions or comments?

Call toll free 1-888-795-4747

PRINCIPAL DISPLAY PANEL - 8 g Jar Label

bareMinerals®

ORIGINAL FOUNDATION
Broad Spectrum SPF 15

FAIRLY MEDIUM 05

net wt. 8 g / 0.28 oz.

61270